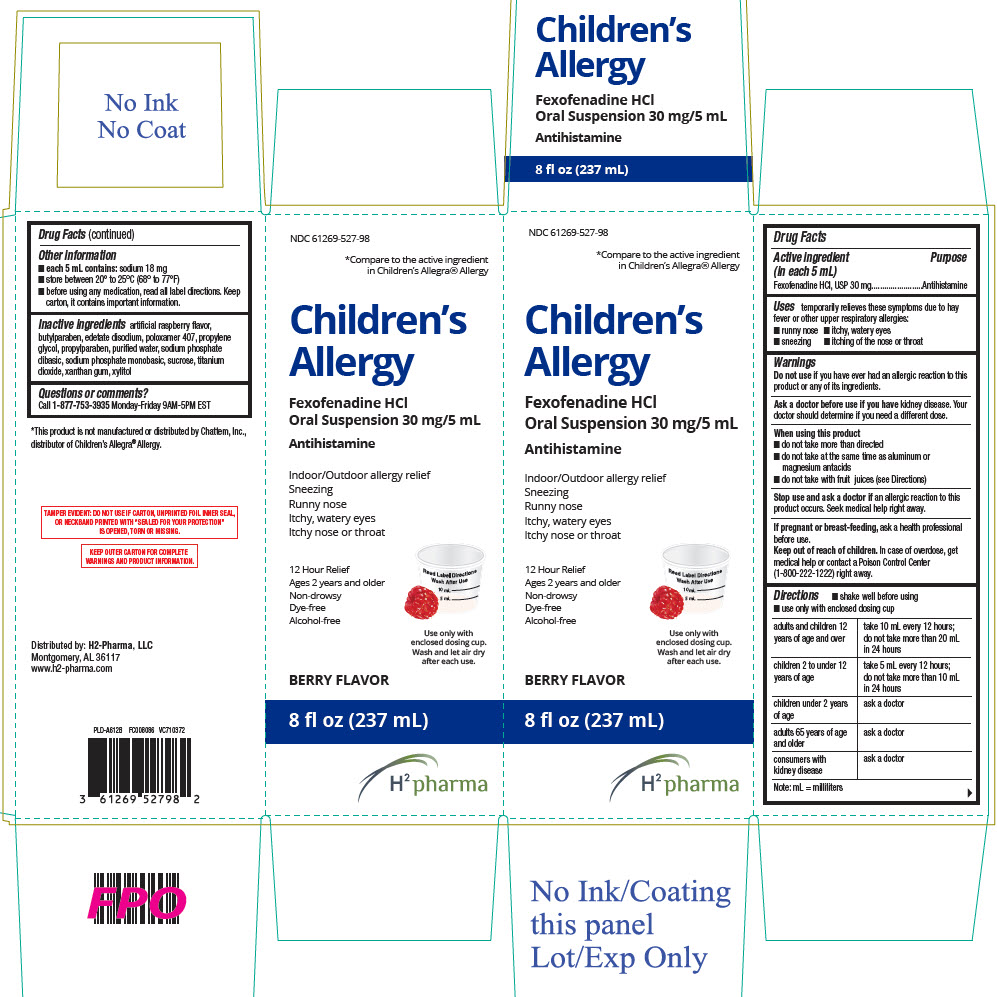 DRUG LABEL: Childrens Allergy
NDC: 61269-527 | Form: SUSPENSION
Manufacturer: H2-Pharma, LLC
Category: otc | Type: HUMAN OTC DRUG LABEL
Date: 20250708

ACTIVE INGREDIENTS: FEXOFENADINE HYDROCHLORIDE 30 mg/5 mL
INACTIVE INGREDIENTS: BUTYLPARABEN; EDETATE DISODIUM; POLOXAMER 407; PROPYLENE GLYCOL; PROPYLPARABEN; WATER; SODIUM PHOSPHATE, DIBASIC, ANHYDROUS; SODIUM PHOSPHATE, MONOBASIC, ANHYDROUS; SUCROSE; TITANIUM DIOXIDE; XANTHAN GUM; XYLITOL

Children's Allergy

Drug Facts

Active ingredient (in each 5 mL)

Fexofenadine HCl, USP 30 mg

Purpose

Antihistamine

Uses

temporarily relieves these symptoms due to hay fever or other upper respiratory allergies:

- runny nose
- itchy, watery eyes
- sneezing
- itching of the nose or throat

Warnings

Do not use if you have ever had an allergic reaction to this product or any of its ingredients.

Ask a doctor before use if you have kidney disease. Your doctor should determine if you need a different dose.

When using this product

- do not take more than directed
- do not take at the same time as aluminum or magnesium antacids
- do not take with fruit juices (see Directions)

Stop use and ask a doctor if an allergic reaction to this product occurs. Seek medical help right away.

PREGNANCY OR BREAST FEEDING

If pregnant or breast-feeding, ask a health professional before use.

Keep out of reach of children. In case of overdose, get medical help or contact a Poison Control Center (1-800-222-1222) right away.

Directions

- shake well before using
- use only with enclosed dosing cup

adults and children 12 years of age and over | take 10 mL every 12 hours; do not take more than 20 mL in 24 hours
children 2 to under 12 years of age | take 5 mL every 12 hours; do not take more than 10 mL in 24 hours
children under 2 years of age | ask a doctor
adults 65 years of age and older | ask a doctor
consumers with kidney disease | ask a doctor
Note: mL = milliliters

Other information

- each 5 mL contains: sodium 18 mg
- store between 20° to 25°C (68° to 77°F)
- before using any medication, read all label directions. Keep carton, it contains important information.

Inactive ingredients

artificial raspberry flavor, butylparaben, edetate disodium, poloxamer 407, propylene glycol, propylparaben, purified water, sodium phosphate dibasic, sodium phosphate monobasic, sucrose, titanium dioxide, xanthan gum, xylitol

Questions or comments?

Call 1-877-753-3935 Monday-Friday 9AM-5PM EST

Distributed by: H2-Pharma, LLC
Montgomery, AL 36117

PRINCIPAL DISPLAY PANEL - 237 mL Bottle Carton

NDC 61269-527-98

*Compare to the active ingredient
in Children's Allegra® Allergy

Children's
Allergy

Fexofenadine HCl
Oral Suspension 30 mg/5 mL

Antihistamine

Indoor/Outdoor allergy relief
Sneezing
Runny nose
Itchy, watery eyes
Itchy nose or throat

12 Hour Relief
Ages 2 years and older
Non-drowsy
Dye-free
Alcohol-free

Use only with
enclosed dosing cup.
Wash and let air dry
after each use.

BERRY FLAVOR

8 fl oz (237 mL)

H^2 pharma